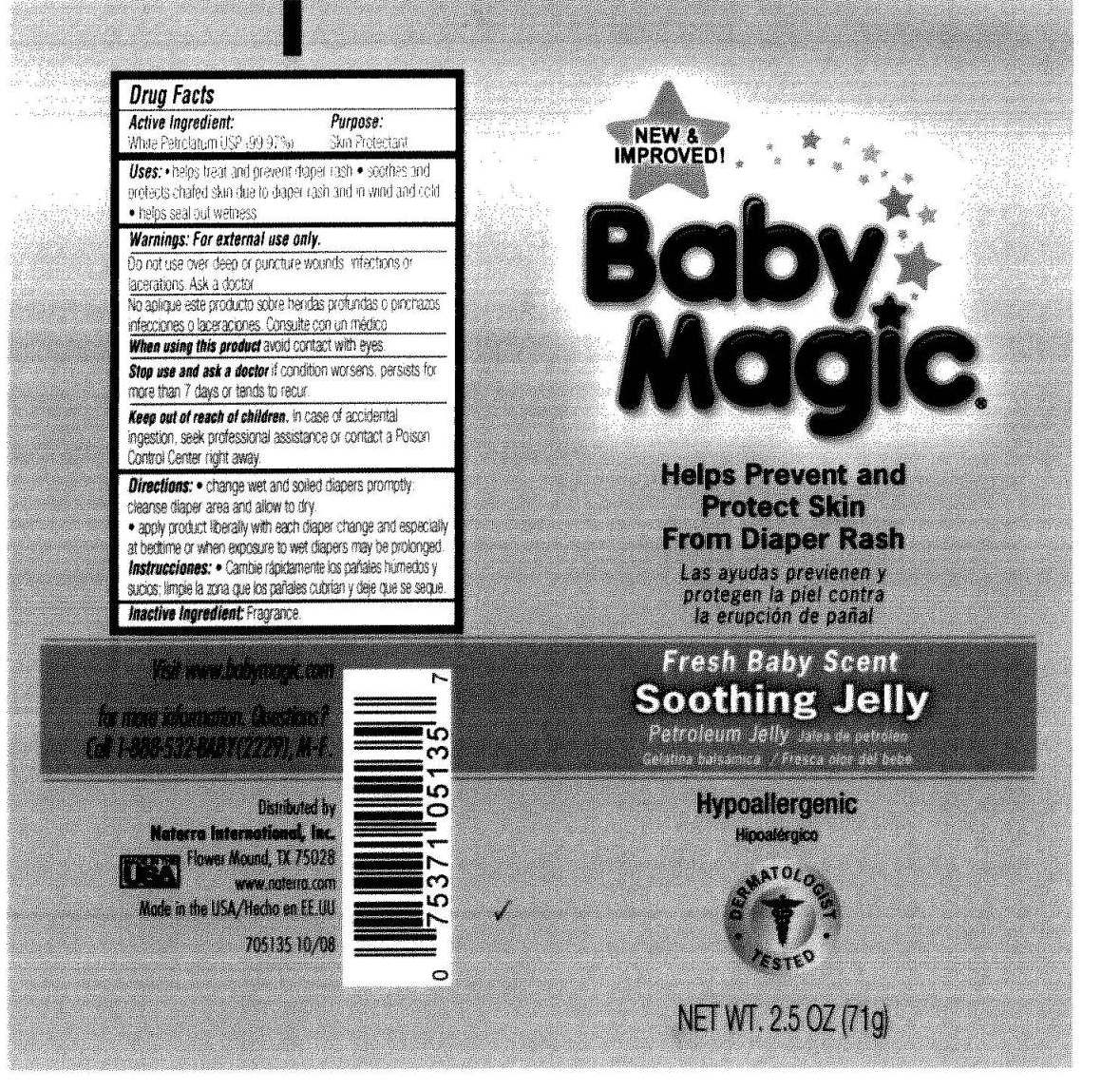 DRUG LABEL: Fresh Baby Scent Soothing Jelly
NDC: 45765-5135 | Form: GEL
Manufacturer: Naterra  International INC.
Category: otc | Type: HUMAN OTC DRUG LABEL
Date: 20110214

ACTIVE INGREDIENTS: PETROLATUM 70.9787 g/71 g
INACTIVE INGREDIENTS: JUNIPERUS VIRGINIANA OIL

Active Ingredient: White Petrolatum USP (99.7%)

Purpose : Skin Protectant

Warnings: For external use only

Do not use over deep or puncture wounds , infections or lacerations. Ask doctor.

Keep out of reach of children
In case of accidental ingestion ,seek professional assistance or contact a Poison Control Center right away.

Directions :
change wet and solied diapers promply; cleanse diaper area and allow to dry.
apply product liberally with each diaper change and especially at bedtime or when exposure to wet diapers may be prolonged.

DOSAGE AND ADMINISTRATION

Uses: helps treat and prevent diaper rash

soothes and protects chafed skin due to diaper rash and in wind and cold

helps seal out wetness

INACTIVE INGREDIENT

Fragrance